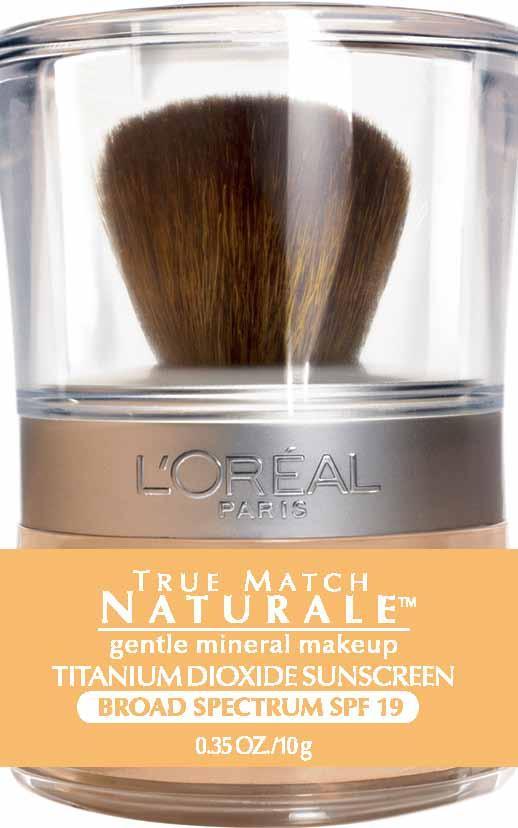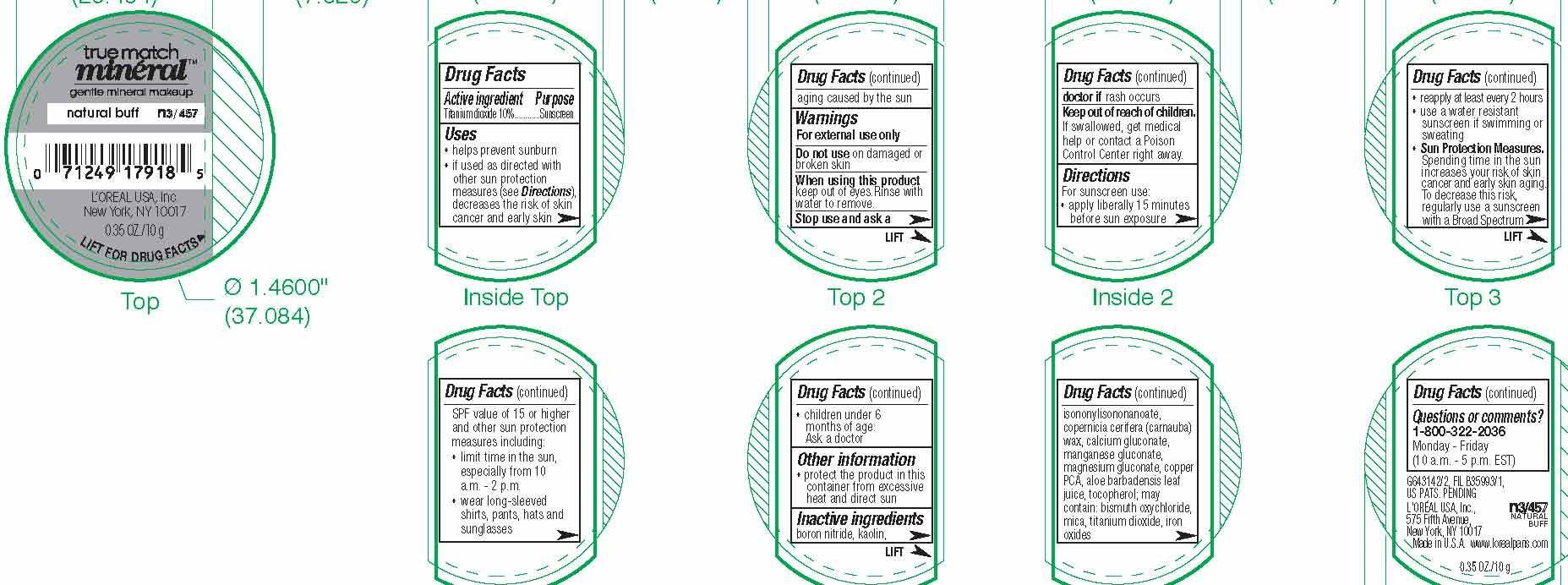 DRUG LABEL: LOreal Paris True Match Naturale gentle mineral makeup Broad Spectrum SPF 19
NDC: 49967-425 | Form: POWDER
Manufacturer: L'Oreal USA Products Inc
Category: otc | Type: HUMAN OTC DRUG LABEL
Date: 20240102

ACTIVE INGREDIENTS: TITANIUM DIOXIDE 100 mg/1 g
INACTIVE INGREDIENTS: BORON NITRIDE; KAOLIN; ISONONYL ISONONANOATE; CARNAUBA WAX; CALCIUM GLUCONATE; MANGANESE GLUCONATE; MAGNESIUM GLUCONATE; COPPER PIDOLATE; ALOE VERA LEAF; TOCOPHEROL; BISMUTH OXYCHLORIDE; MICA; FERRIC OXIDE RED

Drug Facts

Active ingredient

Titanium dioxide 10%

Purpose

Sunscreen

Uses

- helps prevent sunburn

- if used as directed with other sun protection measures (see Directions), decreases the risk of skin cancer and early skin aging caused by the sun

Warnings

For external use only

Do not use

on damaged or broken skin

When using this product

keep out of eyes. Rinse with water to remove.

Stop use and ask a doctor if

rash occurs

Keep out of reach of children.

If swallowed, get medical help or contact a Poison Control Center right away.

Directions

For sunscreen use:

● apply liberally 15 minutes before sun exposure

● reapply at least every 2 hours

● use a water resistant sunscreen if swimming or sweating

● Sun Protection Measures. Spending time in the sun increases your risk of skin cancer and early skin aging. To decrease this risk, regularly use a sunscreen with a Broad Spectrum SPF value of 15 or higher and other sun protection measures including:

● limit time in the sun, especially from 10 a.m. – 2 p.m.

● wear long-sleeved shirts, pants, hats, and sunglasses

● children under 6 months of age: Ask a doctor

Other information

protect the product in this container from excessive heat and direct sun

Inactive ingredients

boron nitride, kaolin, isononylisononanoate, copernicia cerifera (carnauba) wax, calcium gluconate, manganese gluconate, magnesium gluconate, copper PCA, aloe barbadensis leaf juice, tocopherol; may contain: bismuth oxychloride, mica, titanium dioxide, iron oxides

Questions or comments?

1-800-322-2036

Monday - Friday

(10 a.m. - 5 p.m. EST)